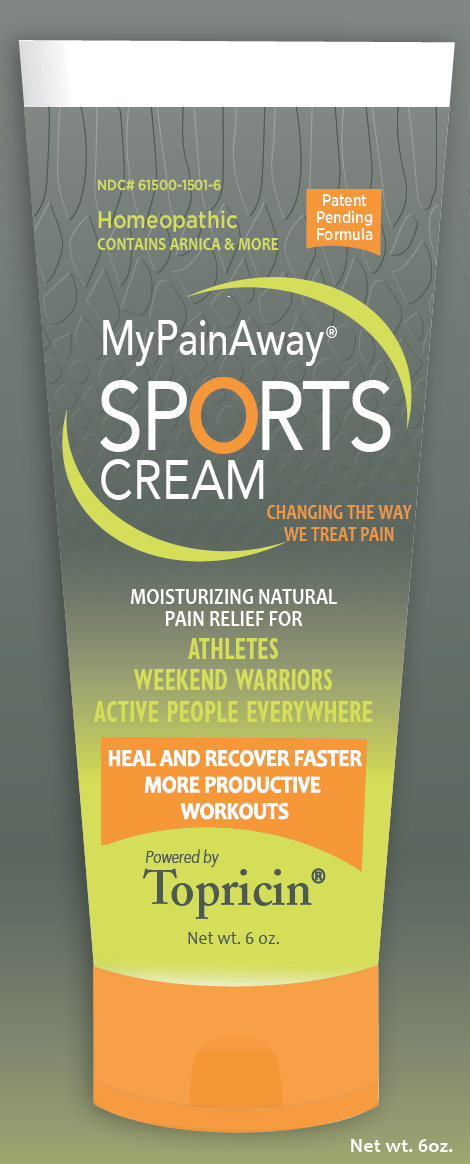 DRUG LABEL: MyPainAway Sports Cream
NDC: 61500-1501 | Form: CREAM
Manufacturer: Topical BioMedics, Inc.
Category: homeopathic | Type: HUMAN OTC DRUG LABEL
Date: 20160205

ACTIVE INGREDIENTS: AESCULUS HIPPOCASTANUM BARK 6 [hp_X]/1 [hp_X]; ARNICA MONTANA 6 [hp_X]/1 [hp_X]; BELLIS PERENNIS 6 [hp_X]/1 [hp_X]; CALENDULA OFFICINALIS WHOLE 6 [hp_X]/1 [hp_X]; SULFUR 8 [hp_X]/1 [hp_X]; CAPSICUM ANNUUM WHOLE 10 [hp_X]/1 [hp_X]; CROTALUS HORRIDUS HORRIDUS WHOLE 8 [hp_X]/1 [hp_X]; ECHINACEA, UNSPECIFIED 6 [hp_X]/1 [hp_X]; GRAPHITE 6 [hp_X]/1 [hp_X]; GELSEMIUM SEMPERVIRENS WHOLE 8 [hp_X]/1 [hp_X]; HYPERICUM PERFORATUM 6 [hp_X]/1 [hp_X]; LACHESIS MUTA WHOLE 8 [hp_X]/1 [hp_X]; POTASSIUM CARBONATE 8 [hp_X]/1 [hp_X]; MAGNESIUM PHOSPHATE, MONOBASIC, UNSPECIFIED 6 [hp_X]/1 [hp_X]; NAJA NAJA WHOLE 8 [hp_X]/1 [hp_X]; RHUS SPP. WHOLE 12 [hp_X]/1 [hp_X]; RUTA GRAVEOLENS WHOLE 6 [hp_X]/1 [hp_X]
INACTIVE INGREDIENTS: CETYL ALCOHOL; GLYCERIN; PALM KERNEL OIL; ISOPROPYL MYRISTATE; WATER; SODIUM HYDROXIDE; STEARETH-21; CAPRYLHYDROXAMIC ACID; GLYCERYL CAPRYLATE; HYDROGENATED PALM KERNEL OIL; GLYCERYL STEARATE SE; CARBOMER INTERPOLYMER TYPE A (ALLYL SUCROSE CROSSLINKED); CETEARETH-12; CETOSTEARYL ALCOHOL; PEG-40 STEARATE

MyPainAway Sports Cream 6 oz.

Drug Facts - Active Ingredients Section with Purpose

Active Ingredients: | Purpose
Aesculus Hippocastanum 6X . . . . | For lower back pain, bruising injuries to hip and spine, muscle and joint impact pain
Arnica Montana 6X . . . . . . | Relieves muscle and joint impact pain
Bellis Perennis 6X . . . . . . | For bruises to nerves, muscle soreness & sprains
Calendula Officinalis 6X . . . . . | Promotes rapid healing of chapped, dry, irritated skin
Capsicum Annum 10X. . . . . . | Teats muscle spasms and sciatica
Crotalus Horridus 8X . . . . . | Relief of swelling impact injury & deep tissue bruising
Echinacea 6X . . . . . | Helps detoxify pain site of excess fluids
Gelsemium Sempervirens 8X . . . . | For muscle cramps & fatigue
Graphites 6X . . . . . | Treats and prevents skin onditions & scarring
Hypericum Perforatum 6X . . . . | For nerve injuries, burning pain and trauma injuries
Kali Carbonicum 8X . . . . | Treats sharp tearing pain in nerves, muscles and relaxes muscle tension
Lachesis Mutus 8X . . . . . | Relieves sudden sharp pain in joints & muscles
Magnesium Phosphorica 6X . . . . | Treats muscle cramps and weakness
Naja Tripudians 8X . . . . | Relieves pain of nerve inuries and swelling
Rhus Tox 12X . . . . . | For burning pain, muscle tension, joint pain and stiffness
Ruta Graveolens 6X . . . . | Relieves pain, soreness and bruising of the hands, wrists and shoulders
Sulphur 8X . . . . . | Relieves inching, cracked skin, rashes & blisters

Purpose

For lower back pain, bruising injuries to hip and spine, muscle and joint impact pain

Relieves muscle and joint impact pain

For bruises to nerves, muscle soreness & sprains

Promotes rapid healing of chapped, dry, irritated skin

Teats muscle spasms and sciatica

Relief of swelling impact injury & deep tissue bruising

Helps detoxify pain site of excess fluids

For muscle cramps & fatigue

Treats and prevents skin onditions & scarring

For nerve injuries, burning pain and trauma injuries

Treats sharp tearing pain in nerves, muscles and relaxes muscle tension

Relieves sudden sharp pain in joints & muscles

Treats muscle cramps and weakness

Relieves pain of nerve inuries and swelling

For burning pain, muscle tension, joint pain and stiffness

Relieves pain, soreness and bruising of the hands, wrists and shoulders

Relieves inching, cracked skin, rashes & blisters

Uses

Uses: Rapid, soothing relief of • pain • stiffness •tingling or burning nerve pain • Sports injuries • muscle pulls and soreness • impact injuries • sprains • dislocations • repetitive motion injuries: • bursitis • tendonitis • sciatica

Warnings

Warnings: Use only as directed • For external use only • Do not apply in eyes.

Ask a doctor or pharmacist if • pain lasts more than 3 days • new symptoms occur • redness or swelling could indiate a more serious condition

Always consult a doctor • before beginning a self-help regimen • if you are taking a prescription medicine.

KEEP OUT OF REACH OF CHILDREN.

If swallowed, seek professional assistance and contact a Poison Control Center right away.

Inactive Ingredients

Captex 300 (from coconut fatty acids); Carbopol® Ultrez 10 (from sucrose); Cetyl Alcohol (from coconut oil); Spectrastat G 2 (derived from coconut); Glycerine (vegetable-based); Hydrokote (palm kernel oil with lecithin); Isopropyl Myristate emollient (from palm seeds); Lipomulse (from coconut fatty acids); Purified Water; Sodium hydroxide; Steareth-21 (from stearic acid cocoa butter)

Other Information

Store at 15° to 30° C (59° to 86° F). Tamper Evident. Do not use if seal is broken or tube is open. • If not completely satisfied within 30 days, return to the point of purchase with receipt for a full refund.

Directions

• Generously apply 3-4 times daily or more often if needed, 3 inches on and around affected area. • Massage in until absorbed. reapply before bedtime and in the morning. • Use before and after physical activity. • Apply immediately for acute trauma injuries (sprain, strain, bruise and impact injuries).

Principal Display Panel

NDC# 61500-1501-6

Homeopathic

contains arnica & more

Patent Pending Formula

MyPainAway(r)

SPORTS

CREAM

CHANGING THE WAY WE TREAT PAIN

MOISTURINZING NATURAL PAIN RELIEF FOR

ATHLETES

WEEKEND WARRIORS

ACTIVE PEOPLE EVERYWHERE

HEAL AND RECOVER FASTER

MORE PRODUCTIVE

WORKOUTS

Powered by Topricin(r)

Net wt. 6 oz.